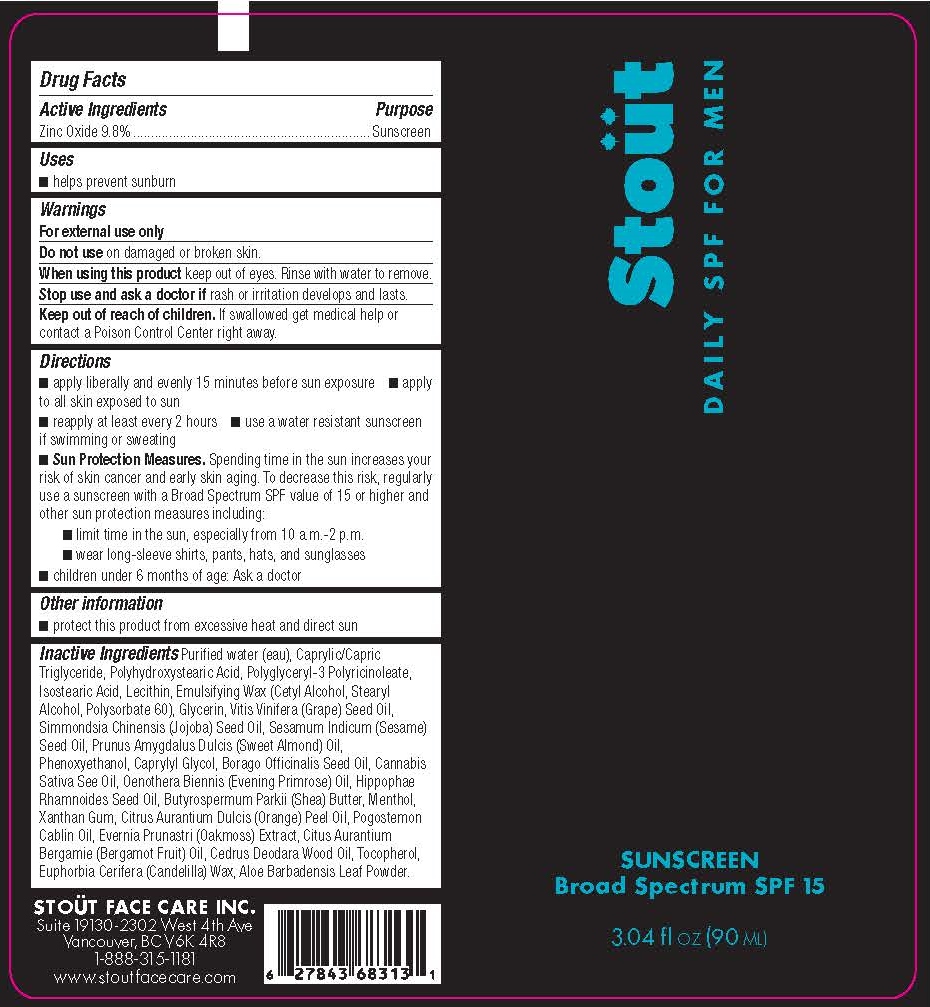 DRUG LABEL: Stout Daily SPF for Men
NDC: 71100-001 | Form: LIQUID
Manufacturer: Stout Face Care Inc.
Category: otc | Type: HUMAN OTC DRUG LABEL
Date: 20170301

ACTIVE INGREDIENTS: ZINC OXIDE 8.82 g/90 mL
INACTIVE INGREDIENTS: WATER; MEDIUM-CHAIN TRIGLYCERIDES; POLYHYDROXYSTEARIC ACID (2300 MW); ISOSTEARIC ACID; CETYL ALCOHOL; STEARYL ALCOHOL; POLYSORBATE 60; GLYCERIN; GRAPE SEED OIL; JOJOBA OIL; SESAME OIL; ALMOND OIL; PHENOXYETHANOL; CAPRYLYL GLYCOL; BORAGE SEED OIL; CANNABIS SATIVA SEED OIL; EVENING PRIMROSE OIL; HIPPOPHAE RHAMNOIDES SEED OIL; SHEA BUTTER; MENTHOL; XANTHAN GUM; CITRUS SINENSIS SEED OIL; PATCHOULI OIL; EVERNIA PRUNASTRI; BERGAMOT OIL; CEDRUS DEODARA WOOD OIL; TOCOPHEROL; CANDELILLA WAX; ALOE VERA LEAF

ACTIVE INGREDIENT

Zinc Oxide 9.8%

PURPOSE

Zinc Oxide 9.8%............................Sunscreen

INDICATIONS AND USAGE

- Helps prevent sunscreen

WARNINGS

For external use only

Do not use on damaged or broken skin.

When using this product keep out of eyes. Rinse with water to remove.

Stop use and ask a doctor if rash or irritation develops and lasts.

Keep out of reach of children. If swallowed get medical help or contact a Poison Control Center right away.

DOSAGE AND ADMINISTRATION

- apply liberally and evenly 15 minutes before sun exposure
- apply to all skin exposed to sun
- reapply at least every 2 hours
- use a water resistant sunscreen if swimming or sweating
- Sun Protection Measures. Spending time in the sun increases your risk of skin cancer and early skin aging. To decrease this risk, regularly use a sunscreen with a Broad Spectrum SPF value of 15 or higher and other sun protection measures including:

○ limit time in the sun, especially from 10 a.m.-2 p.m.

○ wear long-sleeve shirts, pants, hats, and sunglasses

- children under 6 months of age: Ask a doctor

STORAGE AND HANDLING

- protect this product from excessive heat and direct sun

INACTIVE INGREDIENT

Purified water (eau), Caprylic/Capric Triglyceride, Polyhydroxystearic Acid, Polyglyceryl-3 Polyricinoleate, Isostearic Acid, Lecithin, Emulsifying Wax (Cetyl Alcohol, Stearyl Alcohol, Polysorbate 60), Glycerin, Vitis Vinifera (Grape) Seed Oil, Simmondsia Chinensis (Jojoba) Seed Oil, Sesamum Indicum (Sesame) Seed Oil, Prunus Amygdalus Dulcis (Sweet Almond) Oil, Phenoxyethanol, Caprylyl Glycol, Borago Officinalis Seed Oil, Cannabis Sativa Seed Oil, Oenothera Biennis (Evening Primrose) Oil, Hippophae Rhamnoides Seed Oil, Butyrospermum Parkii (Shea) Butter, Menthol, Xanthan Gum, Citrus Aurantium Dulcis (Orange) Peel Oil, Pogostemon Cablin Oil, Evernia Prunastri (Oakmoss) Extract, Citus Aurantium Bergamie (Bergamot Fruit) Oil, Cedrus Deodara Wood Oil, Tocopherol, Euphorbia Cerifera (Candelilla) Wax, Aloe Barbadensis Leaf Powder

DESCRIPTION

STOÜT FACE CARE INC.

Suite 19130-2302 West 4th Ave.

Vancouver, BC V6K 4R8

1-888-315-1181

www.stoutfacecare.com

PACKAGE LABEL

Stoüt

Daily SPF for Men

SUNSCREEN

Broad spectrum SPF 15

3.04 fl oz (90mL)